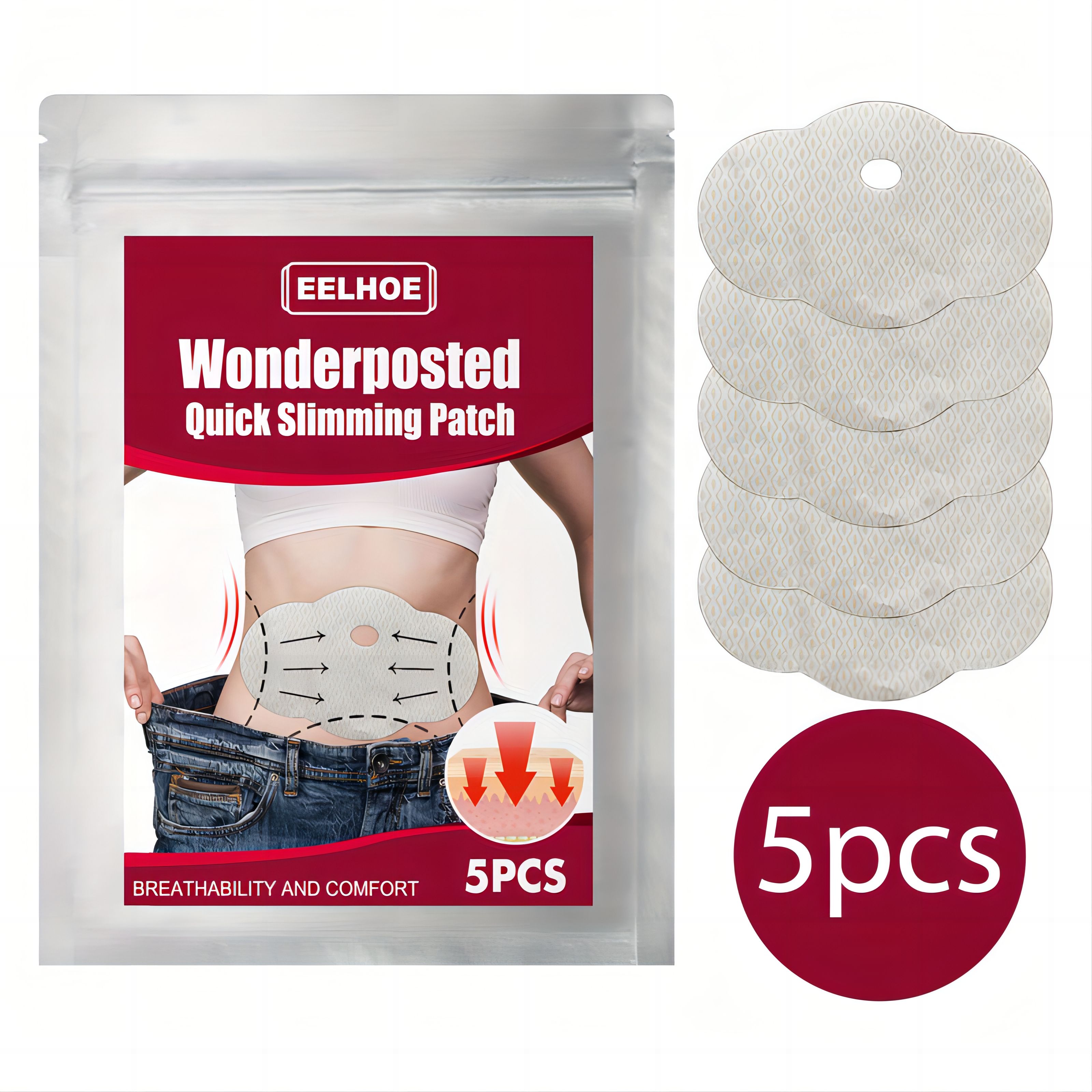 DRUG LABEL: Wonderposted Quick Slimming Patch
NDC: 83675-027 | Form: PATCH
Manufacturer: Guangzhou Hanhai Trading Co., Ltd
Category: otc | Type: HUMAN OTC DRUG LABEL
Date: 20231008

ACTIVE INGREDIENTS: ARTEMISIA VULGARIS WHOLE 29 g/100 1
INACTIVE INGREDIENTS: CINNAMOMUM CASSIA TWIG

Active Ingredient

Mugwort 29.0%

Purpose

Slimming

Use

Eliminate edema
Tighten the arm
Slender and smooth

Warnings

For external use only. Do not take it internally.

Keep Out Of Reach Of Children
Sensitive Skin

Do not use

Product shall not be eat

When Using

1.Clean the target area. Peel off adhesive and apply the patch.
2.Stick it on the body where you need it and keep it for 2-4 hours
These healing magnets do not lose strength over time and can be reused on new replacement castings.

Stop Use

In case of adverse reactions, please stop using this product.If the symptoms.

Ask Doctor

ask doctor in case of Sensitive Skin

Keep Oot Of Reach Of Children

Directions

1.Clean the target area. Peel off adhesive and apply the patch.
2.Stick it on the body where you need it and keep it for 2-4 hours
These healing magnets do not lose strength over time and can be reused on new replacement castings.

Other information

Store the product in a cool, dry and well-ventilated place

Avoid direct sunlight

Inactive ingredients

Cassia Twig